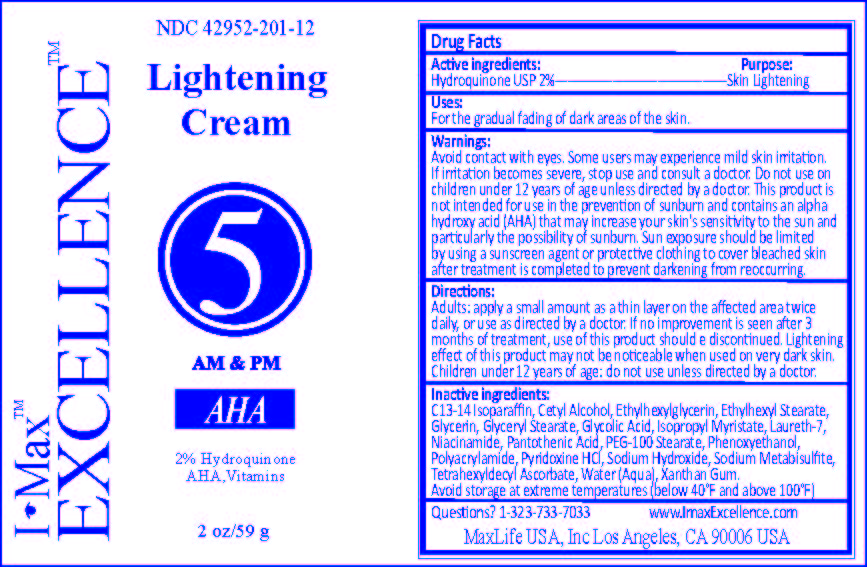 DRUG LABEL: I-MAX LIGHTENING 5
NDC: 42952-201 | Form: CREAM
Manufacturer: MAXLIFE USA, INC.
Category: otc | Type: HUMAN OTC DRUG LABEL
Date: 20181009

ACTIVE INGREDIENTS: HYDROQUINONE 2 g/100 g
INACTIVE INGREDIENTS: C13-14 ISOPARAFFIN; CETYL ALCOHOL; ETHYLHEXYLGLYCERIN; ETHYLHEXYL STEARATE; GLYCERIN; GLYCERYL MONOSTEARATE; GLYCOLIC ACID; ISOPROPYL MYRISTATE; LAURETH-7; NIACINAMIDE; PANTOTHENIC ACID; PEG-100 STEARATE; PHENOXYETHANOL; POLYACRYLAMIDE (10000 MW); PYRIDOXINE HYDROCHLORIDE; SODIUM HYDROXIDE; SODIUM METABISULFITE; TETRAHEXYLDECYL ASCORBATE; WATER; XANTHAN GUM

ACTIVE INGREDIENTS:
HYDROQUINONE USP 2%

PURPOSE:

SKIN LIGHTENING

USES:

FOR THE GRADUAL FADING OF DARK AREAS OF THE SKIN.

WARNINGS:

AVOID CONTACT WITH EYES. SOME USERS MAY EXPERIENCE MILD SKIN IRRITATION.

STOP USE

IF IRRITATION BECOMES SEVERE, STOP USE AND CONSULT A DOCTOR.

OTHER SAFETY INFORMATION

THIS PRODUCT IS NOT INTENDED FOR USE IN THE PREVENTION OF SUNBURN AND CONTAINS AN ALPHA HYDROXY ACID (AHA) THAT MAY INCREASE YOUR SKIN'S SENSITIVITY TO THE SUN AND PARTICULARLY THE POSSIBILITY OF SUNBURN. SUN EXPOSURE SHOULD BE LIMITED BY USING A SUNSCREEN AGENT OR PROTECTIVE CLOTHING TO COVER BLEACHED SKIN AFTER TREATMENT IS COMPLETED TO PREVENT DARKENING FROM REOCCURING.

DO NOT USE ON CHILDREN UNDER 12 YEARS OF AGE UNLESS DIRECTED BY A DOCTOR.

DIRECTIONS:

ADULTS: APPLY A SMALL AMOUNT AS A THIN LAYER ON THE AFFECTED AREA TWICE DAILY, OR USE AS DIRECTED BY A DOCTOR. IF NO IMPROVEMENT IS SEEN AFTER 3 MONTHS OF TREATMENT, USE OF THIS PRODUCT SHOULD BE DISCONTINUED. LIGHTENING EFFECT OF THIS PRODUCT MAY NOT BE NOTICEABLE WHEN USED ON VERY DARK SKIN.

CHILDREN UNDER 12 YEARS OF AGE: DO NOT USE UNLESS DIRECTED BY A DOCTOR.

INACTIVE INGREDIENTS:

C13-14 ISOPARAFFIN, CETYL ALCOHOL, ETHYLHEXYLGLYCERIN, ETHYLHEXYL STEARATE, GLYCERIN, GLYCERYL STEARATE, GLYCOLIC ACID, ISOPROPYL MYRISTATE, LAURETH-7, NIACINAMIDE, PANTOTHENIC ACID, PEG-100 STEARATE, PHENOXYETHANOL, POLYACRYLAMIDE, PYRIDOXINE HCL, SODIUM HYDROXIDE, SODIUM METABISULFITE, TETRAHEXYLDECYL ASCORBATE, WATER (AQUA), XANTHAN GUM.

QUESTIONS? 1-323-733-7033

KEEP OUT OF REACH OF CHILDREN.